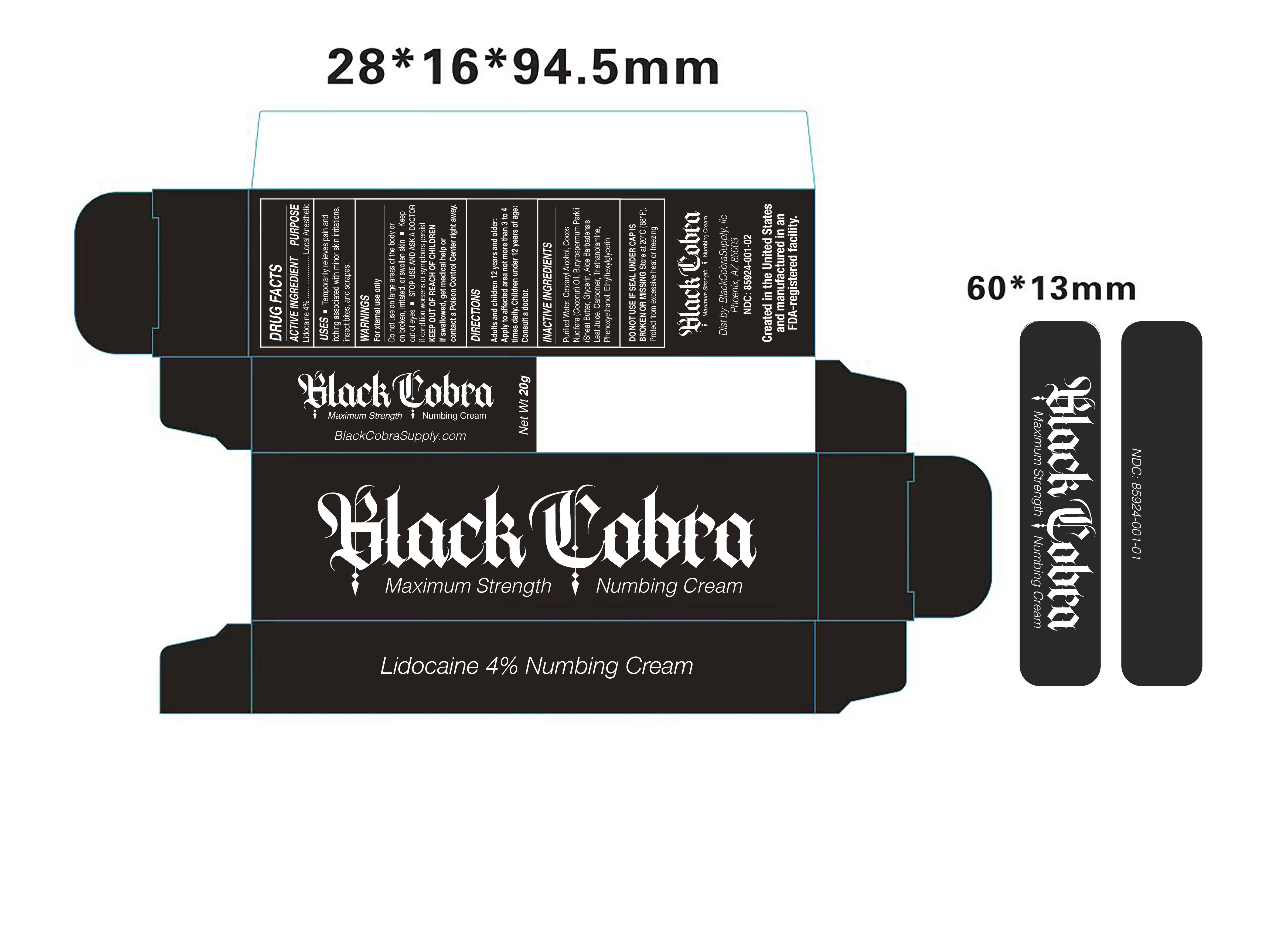 DRUG LABEL: Black Cobra 4% Lidocaine Numbing Cream
NDC: 85924-001 | Form: CREAM
Manufacturer: BLACKCOBRASUPPLY, LLC
Category: otc | Type: HUMAN OTC DRUG LABEL
Date: 20250811

ACTIVE INGREDIENTS: LIDOCAINE 40 mg/1 g
INACTIVE INGREDIENTS: BENZYL ALCOHOL; STEARYL ALCOHOL; SODIUM HYDROXIDE; PROPYLENE GLYCOL; CETYL ALCOHOL; CARBOMER 1342; WATER; GLYCERIN

Purpose

Topical anesthetic

Uses

Temporarily relieves pain and itching due to minor cuts, scrapes, burns, insect bites, and skin irritations.

Warnings

For external use only.
Avoid contact with eyes.
Do not use:
• on large areas of the body
• on broken or blistered skin
• for more than 7 days unless directed by a doctor
Stop use and ask a doctor if:
• condition worsens
• symptoms persist for more than 7 days or clear up and occur again within a few days
• redness, irritation, swelling, or pain persists or increases
Keep out of reach of children. If swallowed, get medical help or contact a Poison Control Center right away.

Dosage and Administration

Adults and children 12 years and older:
• Apply a thin layer to affected area not more than 3 to 4 times daily.
Children under 12 years:
• Consult a doctor before use.

Inactive Ingredients

Purified Water, Propylene Glycol, Glycerin, Cetyl Alcohol, Stearyl Alcohol, Carbomer 1342, Benzyl Alcohol, Sodium Hydroxide.

Keep Out of Reach of Children

If swallowed, get medical help or contact a Poison Control Center right away.

Black Cobra 4% Lidocaine Numbing Cream – Principal Display Panel

See image below.